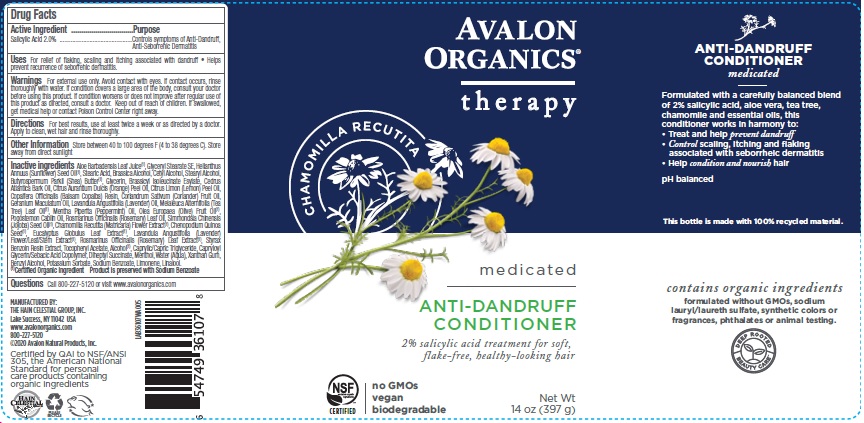 DRUG LABEL: Avalon Organics Antidandruff Conditioner
NDC: 61995-1607 | Form: RINSE
Manufacturer: The Hain Celestial Group, Inc.
Category: otc | Type: HUMAN OTC DRUG LABEL
Date: 20250711

ACTIVE INGREDIENTS: SALICYLIC ACID 2 g/397 g
INACTIVE INGREDIENTS: GLYCERIN; BRASSICA JUNCEA SEED OIL; CHENOPODIUM QUINOA SEED; CAPRYLOYL GLYCERIN/SEBACIC ACID COPOLYMER (2000 MPA.S); ALOE VERA LEAF; WATER; GLYCERYL STEARATE SE; STEARIC ACID; CETYL ALCOHOL; SUNFLOWER OIL; DIHEPTYL SUCCINATE; STEARYL ALCOHOL; OLIVE OIL; JOJOBA OIL; SHEA BUTTER; CHAMOMILE; EUCALYPTUS GLOBULUS LEAF; LAVANDULA ANGUSTIFOLIA FLOWER; MELALEUCA ALTERNIFOLIA LEAF; ROSMARINUS OFFICINALIS FLOWER; STYRAX BENZOIN RESIN; CEDRUS ATLANTICA BARK OIL; ORANGE OIL; LEMON OIL; COPAIFERA OFFICINALIS RESIN; CORIANDER OIL; GERANIUM MACULATUM WHOLE; LAVENDER OIL; MENTHA PIPERITA; POGOSTEMON CABLIN WHOLE; ROSEMARY OIL; MENTHOL; .ALPHA.-TOCOPHEROL ACETATE; XANTHAN GUM; ALCOHOL; BENZYL ALCOHOL; POTASSIUM SORBATE; SODIUM BENZOATE; CAPRYLIC/CAPRIC MONO/DIGLYCERIDES; LINALOOL, (+/-)-; LIMONENE, (+)-

Avalon Organics Anti-Dandruff Conditioner
PF161764-02, F01867
Items AV36107 397g, AV35008 325ml

WARNINGS

For external use only. Avoid contact with eyes. Rinse eyes throughly with water in case contact ossurs. Discontinue to use and contact your physician if irritation develops.

ACTIVE INGREDIENT

Salicylic Acid 2.0%

PURPOSE

Controls symptoms of dandruff, seboric dermatitis and psoriasis

Keep out of reach of children. If swallowed, get medical help or contact Poison Control Center right away.

INDICATIONS AND USAGE

For relief of flaking, scaling and itching associated with dandruff. Helps prevent Seborrheic Dermatitis

DOSAGE AND ADMINISTRATION

For the best results use at least three times each week. Apply to clean, wet hair. Rinse throughly.

INACTIVE INGREDIENT

Aloe Barbadensis Leaf Juice (1), Glyceryl Stearate SE, Helianthus Annuus (Sunflower) Seed Oil (1), Stearic Acid, Brassica Alcohol, Cetyl Alcohol, Stearyl Alcohol, Butyrospermum Parkii (Shea) Butter (1), Glycerin, Brassicyl Isoleucinate Esylate, Cedrus Atlantica Bark Oil, Citrus Aurantium Dulcis (Orange) Peel Oil, Citrus Limon (Lemon) Peel Oil, Copaifera Officinalis (Balsam Copaiba) Resin, Coriandrum Sativum (Coriander) Fruit Oil, Geranium Maculatum Oil, Lavandula Angustifolia (Lavender) Oil, Melaleuca Alternifolia (Tea Tree) Leaf Oil (1), Mentha Piperita (Peppermint) Oil, Olea Europaea (Olive) Fruit Oil (1), Pogostemon Cablin Oil, Rosmarinus Officinalis (Rosemary) Leaf Oil, Simmondsia Chinensis (Jojoba) Seed Oil (1), Chamomilla Recutita (Matricaria) Flower Extract (1), Chenopodium Quinoa Seed (1), Eucalyptus Globulus Leaf Extract (1), Lavandula Angustifolia (Lavender) Flower/Leaf/Stem Extract (1), Rosmarinus Officinalis (Rosemary) Leaf Extract (1), Styrax Benzoin Resin Extract, Tocopheryl Acetate, Alcohol (1), Caprylic/Capric Triglyceride, Capryloyl Glycerin/Sebacic Acid Copolymer, Diheptyl Succinate, Menthol, Water (Aqua), Xanthan Gum, Benzyl Alcohol, Potassium Sorbate, Sodium Benzoate, Limonene, Linalool.

(1) Certified Organic Ingredients